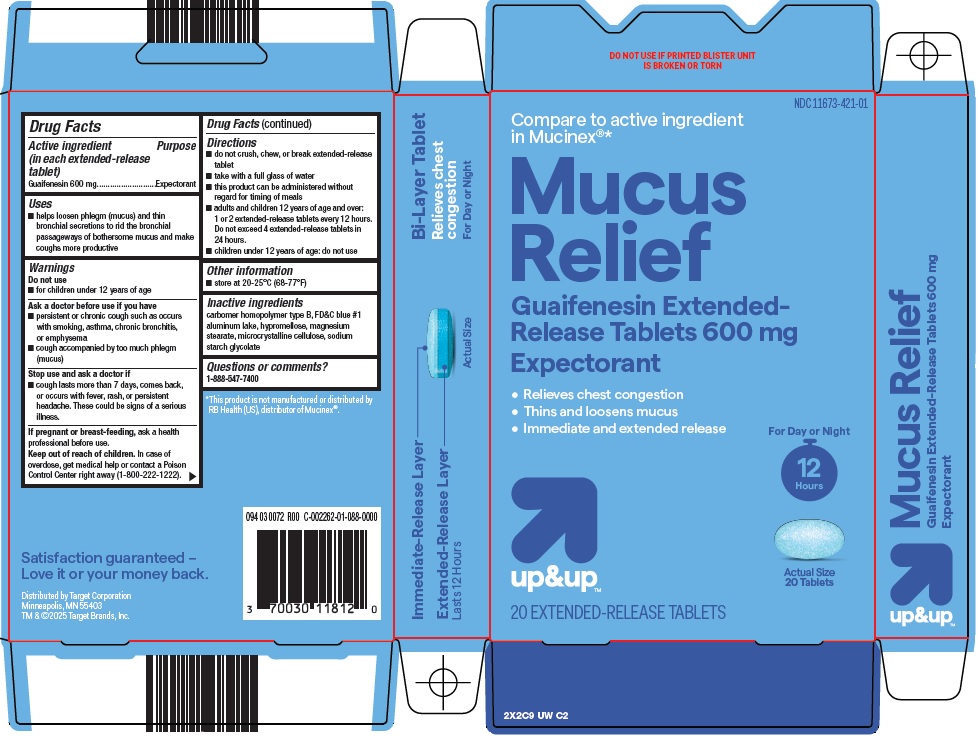 DRUG LABEL: up and up mucus relief
NDC: 11673-421 | Form: TABLET, MULTILAYER, EXTENDED RELEASE
Manufacturer: Target Corporation
Category: otc | Type: HUMAN OTC DRUG LABEL
Date: 20260205

ACTIVE INGREDIENTS: GUAIFENESIN 600 mg/1 1
INACTIVE INGREDIENTS: CARBOMER HOMOPOLYMER TYPE B (ALLYL PENTAERYTHRITOL CROSSLINKED); FD&C BLUE NO. 1 ALUMINUM LAKE; HYPROMELLOSE, UNSPECIFIED; MAGNESIUM STEARATE; MICROCRYSTALLINE CELLULOSE; SODIUM STARCH GLYCOLATE TYPE A

Target Corporation Mucus Relief Drug Facts

Active ingredient (in each extended-release tablet)

Guaifenesin 600 mg

Purpose

Expectorant

Uses

- helps loosen phlegm (mucus) and thin bronchial secretions to rid the bronchial passageways of bothersome mucus and make coughs more productive

Warnings

Do not use

- for children under 12 years of age

Ask a doctor before use if you have

- persistent or chronic cough such as occurs with smoking, asthma, chronic bronchitis, or emphysema
- cough accompanied by too much phlegm (mucus)

Stop use and ask a doctor if

- cough lasts more than 7 days, comes back, or occurs with fever, rash, or persistent headache. These could be signs of a serious illness.

If pregnant or breast-feeding,

ask a health professional before use.

Keep out of reach of children.

In case of overdoes, get medical help or contact a Poison Control Center right away (1-800-222-1222).

Directions

- do not crush, chew, or break extended-release tablet
- take with a full glass of water
- this product can be administered without regard for timing of meals
- adults and children 12 years of age and over: 1 or 2 extended-release tablets every 12 hours. Do not exceed 4 extended-release tablets in 24 hours.
- children under 12 years of age: do not use

Other information

- store between 20-25°C (68-77°F)

Inactive ingredients

carbomer homopolymer type B, FD&C blue #1 aluminum lake, hypromellose, magnesium stearate, microcrystalline cellulose, sodium starch glycolate

Questions or comments?

1-888-547-7400

Package/Label Principal Display Panel

Compare to active ingredient in Mucinex®

Mucus Relief

Guaifenesin Extended-Release Tablets 600 mg

Expectorant

• Relieves chest congestion

• Thins and loosens mucus

• Immediate and extended release

For Day or Night

12 HOURS

up&upTM

Actual Size

20 Tablets

20 EXTENDED-RELEASE TABLETS